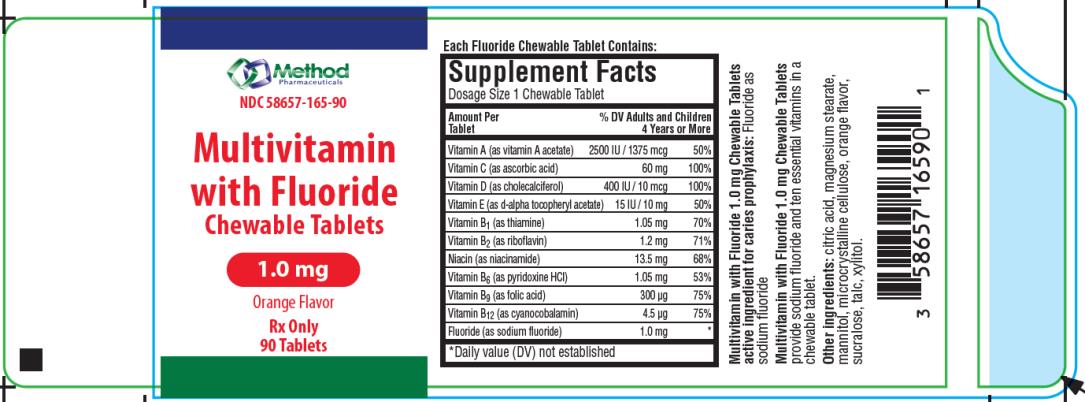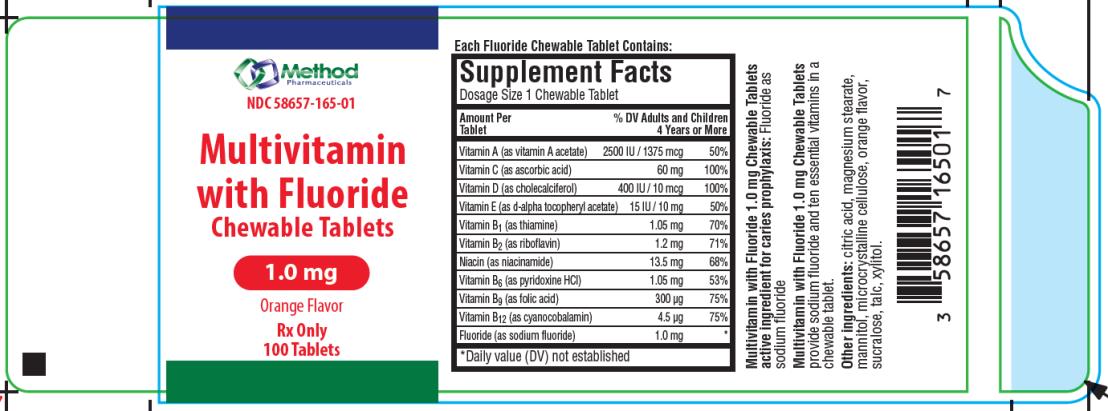 DRUG LABEL: Multivitamin with Fluoride
NDC: 58657-165 | Form: TABLET, CHEWABLE
Manufacturer: Method Pharmaceuticals, LLC
Category: prescription | Type: HUMAN PRESCRIPTION DRUG LABEL
Date: 20251021

ACTIVE INGREDIENTS: VITAMIN A 2500 [iU]/1 1; ASCORBIC ACID 60 mg/1 1; VITAMIN D 400 [iU]/1 1; .ALPHA.-TOCOPHEROL ACETATE, DL- 15 [iU]/1 1; THIAMINE MONONITRATE 1.05 mg/1 1; RIBOFLAVIN 1.2 mg/1 1; NIACIN 13.5 mg/1 1; PYRIDOXINE 1.05 mg/1 1; FOLIC ACID 300 ug/1 1; CYANOCOBALAMIN 4.5 ug/1 1; SODIUM FLUORIDE 1 mg/1 1
INACTIVE INGREDIENTS: CITRIC ACID MONOHYDRATE; MAGNESIUM STEARATE; MANNITOL; CELLULOSE, MICROCRYSTALLINE; SUCRALOSE; TALC; XYLITOL

Multivitamin with Fluoride 1 mg

MULTIVITAMIN WITH FLUORIDE

Disclaimer: This drug has not been found by FDA to be safeand effective, and this labeling has not been approved by FDA.

Prescribing Information

Each Fluoride Chewable Tablet Contains:

Supplement Facts

Dosage Size 1 Chewable Tablet

 | Amount per Tablet | % DV Adults and Children
 |  | 4 years or More
Vitamin A (as Vitamin A acetate) | 2500 IU | 50%
Vitamin C (as ascorbic acid) | 60 mg | 100%
Vitamin D (as cholecalciferol) | 400 IU | 100%
Vitamin E (dl-alpha tocopherol acetate) | 15 IU | 50%
Thiamine (as thiamine) | 1.05 mg | 70%
Riboflavin (as riboflavin) | 1.2 mg | 71%
Niacin (as niacinamide) | 13.5 mg | 68%
Vitamin B6 (as pyridoxine HCl) | 1.05 mg | 53%
Folate (as folic acid) | 300 mcg | 75%
Vitamin B12 (as cyanocobalamin) | 4.5 mcg | 75%
Fluoride (as sodium fluoride) | 1.0 mg | *

*Daily value (DV) not established

Multivitamin with Fluoride 1.0 mg Chewable Tabletsactive ingredient for caries prophylaxis: Fluoride as sodium fluoride

Multivitamin with Fluoride 1.0 mg Chewable Tabletsprovide sodium fluoride and ten essential vitamins in a chewable tablet.

Other ingredients: citric acid, magnesium stearate, mannitol, microcrystalline cellulose, orange flavor, sucralose, talc, xylitol.

CLINICAL PHARMACOLOGY

It is well established that fluoridation of the water supply (1 ppm fluoride) during the period of tooth development leads to a significant decrease in the incidence of dental caries.

Multivitamin with Fluoride 1.0 mg Chewable Tablets provide sodium fluoride and ten essential vitamins in a chewable tablet. Because the tablets are chewable, they provide a topical as well as systemic source of fluoride. Hydroxyapatite is the principal crystal for all calcified tissue in the human body. The fluoride ion reacts with the hydroxyapatite in the tooth as it is formed to produce the more caries-resistant crystal, fluorapatite. The reaction may be expressed by the equation:

Ca10(PO4)6(OH)2 + 2F- ------- Ca10(PO4)6F2 + 2OH-

(Hydroxyapatite) (Fluorapatite)

Three stages of fluoride deposition in tooth enamel can be distinguished:

1. Small amounts (reflecting the low levels of fluoride in tissue fluids) are incorporated into the enamel crystals while they are being formed.

2. After enamel has been laid down, fluoride deposition continues in the surface enamel. Diffusion of fluoride from the surface inward is apparently restricted.

3. After eruption, the surface enamel acquires fluoride from the water, food, supplementary fluoride and smaller amounts from saliva.

INDICATIONS AND USAGE

Supplementation of the diet with ten essential vitamins.

Supplementation of the diet with fluoride for caries prophylaxis.

Multivitamin with Fluoride 1.0 mg Chewable Tablets provide 1.0 mg fluoride in tablet form for children 6-16 years of age in areas where the water fluoride level is less than 0.3 ppm.

Multivitamin with Fluoride 1.0 mg Chewable Tablets supply significant amounts of Vitamins A, C, D, E, thiamine, riboflavin, niacin, vitamin B6, vitamin B12, and folate to supplement the diet, and to help assure that nutritional deficiencies of these vitamins will not develop.

Thus, in a single easy-to-use preparation, children obtain ten essential vitamins and the important mineral, fluoride. The American Academy of Pediatrics recommends that children up to age 16, in areas where drinking water contains less than optimal levels of fluoride, receive daily fluoride supplements.

Children using Multivitamin with Fluoride 1.0 mg Chewable Tablets regularly should receive semiannual dental examinations. The regular brushing of teeth and attention to good oral hygiene practices are also essential. Multivitamin with Fluoride Chewable Tablets is a prescription product for the clinical dietary management of the metabolic processes of caries prophylaxis and provides supplementation of the diet with ten essential vitamins.

WARNING

Keep out of the reach of children. In case of accidental overdose, seek professional assistance or contact a Poison Control Center immediately.

CAUTION

Do not eat or drink dairy products within one hour of fluoride administration.

Should be chewed. This product, as all chewable tablets, is not recommended for children under age 4 due to risk of choking.

PRECAUTION

The suggested dose of Multivitamin with Fluoride 1.0 mg Chewable Tablets should not be exceeded, since dental fluorosis may result from continued ingestion of large amounts of fluoride.

Before prescribing Multivitamin with Fluoride 1.0 mg

Chewable Tablets:

1. Determine the fluoride content of the drinking water from all major sources.

2. Make sure the child is not receiving significant amounts of fluoride from other sources such as medications and swallowed toothpaste.

3. Periodically check to make sure that the child does not develop significant dental fluorosis.

ADVERSE REACTIONS

Allergic rash and other idiosyncrasies have been rarely reported.

DOSAGE AND ADMINISTRATION

One tablet daily, to be dissolved in the mouth or chewed before swallowing. Do not give a chewable tablet to a child younger than 4 years old.

HOW SUPPLIED

Multivitamin Chewable tablets containing 1.0 mg fluoride are round yellowish/cream tablets with orange and yellow speckles. Debossed with “M165” on one side.

NDC: 58657-165-90 (90 count)

NDC: 58657-165-01 (100 count)

STORAGE

Store at 20°-25°C (68°-77°F); excursions permitted to 15°-30°C (59°-86°F). See USP Controlled Room Temperature.

Dispense in a tight, light resistant container with a child-resistant closure as defined in the USP/NF. All prescription substitutions using this product shall be pursuant to state statutes as applicable. This is not an Orange Book product.

Manufactured For:
Method Pharmaceuticals
Fort Worth, TX 76118
Rev. 06/2019

PRINCIPAL DISPLAY PANEL

NDC 58657-165-90
Multivitamin
with Fluoride
Chewable Tablets
1.0 mg
Orange Flavor
Rx Only
90 Tablets

PRINCIPAL DISPLAY PANEL

NDC 58657-165-01
Multivitamin
with Fluoride
Chewable Tablets
1.0 mg
Orange Flavor
Rx Only
100 Tablets